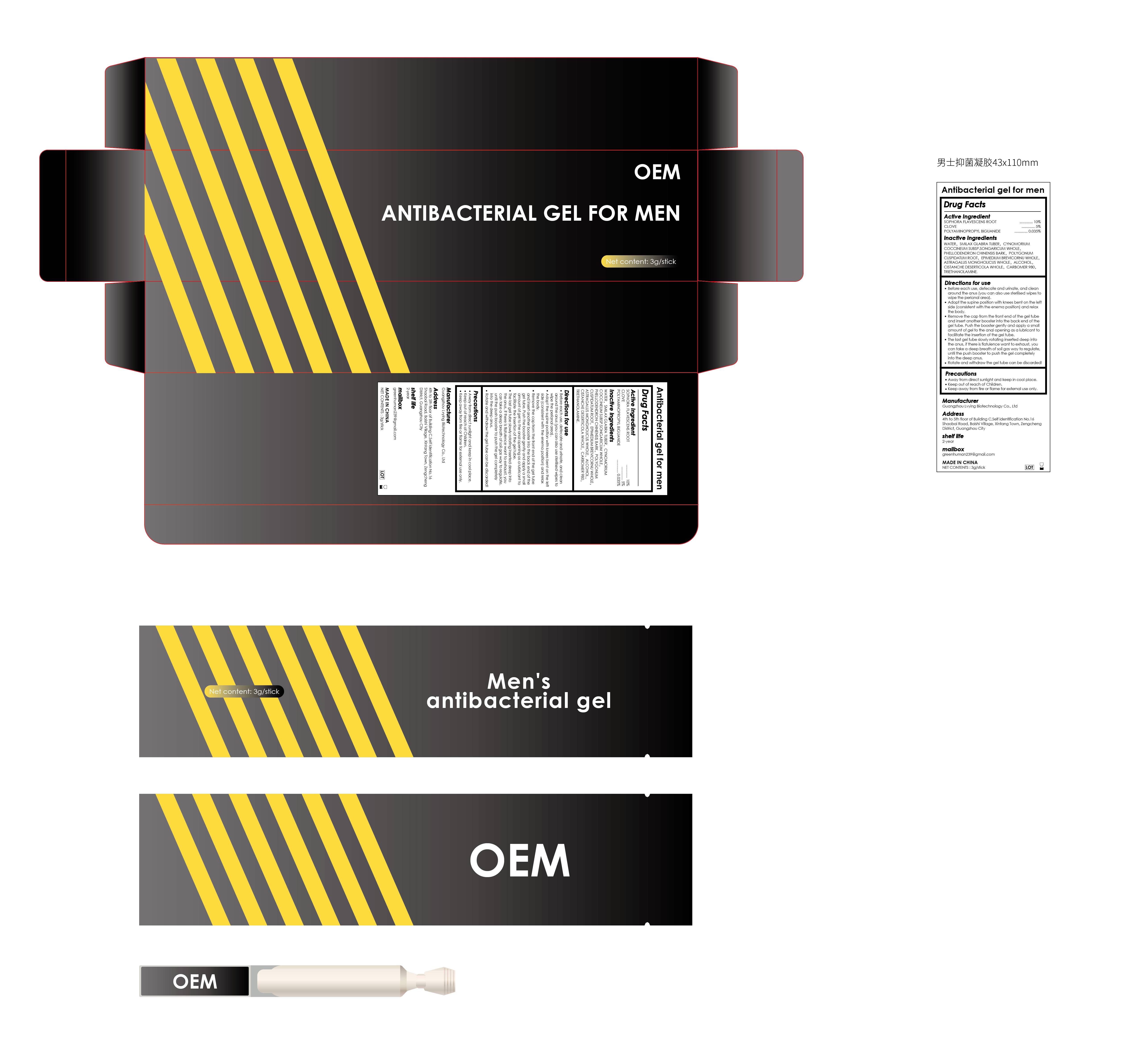 DRUG LABEL: Antibacterial gel for men
NDC: 84260-011 | Form: GEL
Manufacturer: Guangzhou Lvying Biotechnology Co.,Ltd
Category: otc | Type: HUMAN OTC DRUG LABEL
Date: 20250311

ACTIVE INGREDIENTS: CLOVE 5 g/100 g; POLYAMINOPROPYL BIGUANIDE 0.035 g/100 g; SOPHORA FLAVESCENS ROOT 10 g/100 g
INACTIVE INGREDIENTS: SMILAX GLABRA TUBER; PHELLODENDRON CHINENSIS BARK; ALCOHOL; CYNOMORIUM COCCINEUM SUBSP. SONGARICUM WHOLE; TRIETHANOLAMINE; POLYGONUM CUSPIDATUM ROOT; CISTANCHE DESERTICOLA WHOLE; EPIMEDIUM BREVICORNU WHOLE; WATER; ASTRAGALUS MONGHOLICUS WHOLE; CARBOMER 980

Antibacterial gel for men

ACTIVE INGREDIENT

SOPHORA FLAVESCENS ROOT 10%

CLOVE 5%

POLYAMINOPROPYL BIGUANIDE 0.035%

PURPOSE

Antibacterial gel for men

Keep out of reach of children

INDICATIONS AND USAGE

Men's antibacterial gel

WARNINGS

Keep Away fomm fire or Flame for External Use omly

DOSAGE AND ADMINISTRATION

Before each use, defecate and urinate, and clean around the anus (you can also use sterilised wipes to wipe the perianal area).

Adopt the supine position with knees bent on the left side (consistent with the enema position) and relax the body.

Remove the cap from the front end of the gel tube and insert another booster into the back end of the gel tube. Push the booster gently and apply a small amount of gel to the anal opening as a lubricant to facilitate the insertion of the gel tube.

The last gel tube slowly rotating inserted deep into the anus, if there is flatulence want to exhaust, you can take a deep breath of soil gas way to regulate, until the push booster to push the gel completely into the deep anus.

STORAGE AND HANDLING

Away from direct sunlight and keep in cool place.
Keep out of reach of Children.
Keep away from fire or flame for external use only.

INACTIVE INGREDIENT

WATER

SMILAX GLABRA TUBER

CYNOMORIUM COCCINEUM SUBSP.SONGARICUM WHOLE

PHELLODENDRON CHINENSIS BARK

POLYGONUM CUSPIDATUM ROOT

EPIMEDIUM BREVICORNU WHOLE

ASTRAGALUS MONGHOLICUS WHOLE

ALCOHOL

CISTANCHE DESERTICOLA WHOLE

CARBOMER 980

TRIETHANOLAMINE